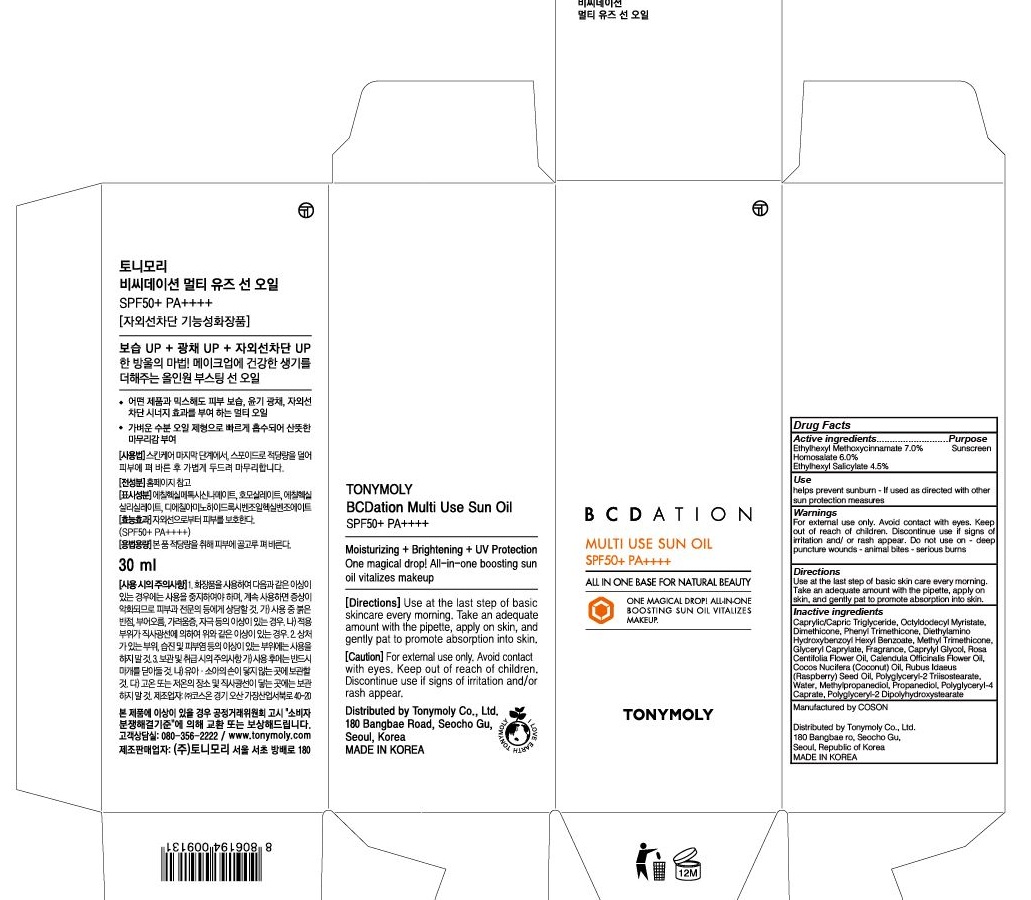 DRUG LABEL: TONYMOLY BCDATION MULTI USE SUN
NDC: 59078-323 | Form: OIL
Manufacturer: TONYMOLY CO.,LTD
Category: otc | Type: HUMAN OTC DRUG LABEL
Date: 20170217

ACTIVE INGREDIENTS: Octinoxate 2.1 g/30 mL; Homosalate 1.8 g/30 mL; Octisalate 1.35 g/30 mL
INACTIVE INGREDIENTS: Octyldodecyl Myristate

ACTIVE INGREDIENT

Active ingredients: Ethylhexyl Methoxycinnamate 7.0%, Homosalate 6.0%, Ethylhexyl Salicylate 4.5%

INACTIVE INGREDIENT

Inactive Ingredients: Caprylic/Capric Triglyceride, Octyldodecyl Myristate, Dimethicone, Phenyl Trimethicone, Diethylamino Hydroxybenzoyl Hexyl Benzoate, Methyl Trimethicone, Glyceryl Caprylate, Fragrance, Caprylyl Glycol, Rosa Centifolia Flower Oil, Calendula Officinalis Flower Oil, Cocos Nucifera (Coconut) Oil, Rubus Idaeus (Raspberry) Seed Oil, Polyglyceryl-2 Triisostearate, Water, Methylpropanediol, Propanediol, Polyglyceryl-4 Caprate, Polyglyceryl-2 Dipolyhydroxystearate

PURPOSE

Purpose: Sunscreen

WARNINGS

Warnings: For external use only. Avoid contact with eyes. Keep out of reach of children. Discontinue use if signs of irritation and/or rash appear. Do not use on - deep puncture wounds - animal bites - serious burns

DESCRIPTION

Use: Helps prevent sunburn - if used as directed with other sun protection measures.

Directions: Use at the last step of basic skin care every morning. Take an adequate amount with the pipette, apply on skin, and gently pat to promote absorption into skin.